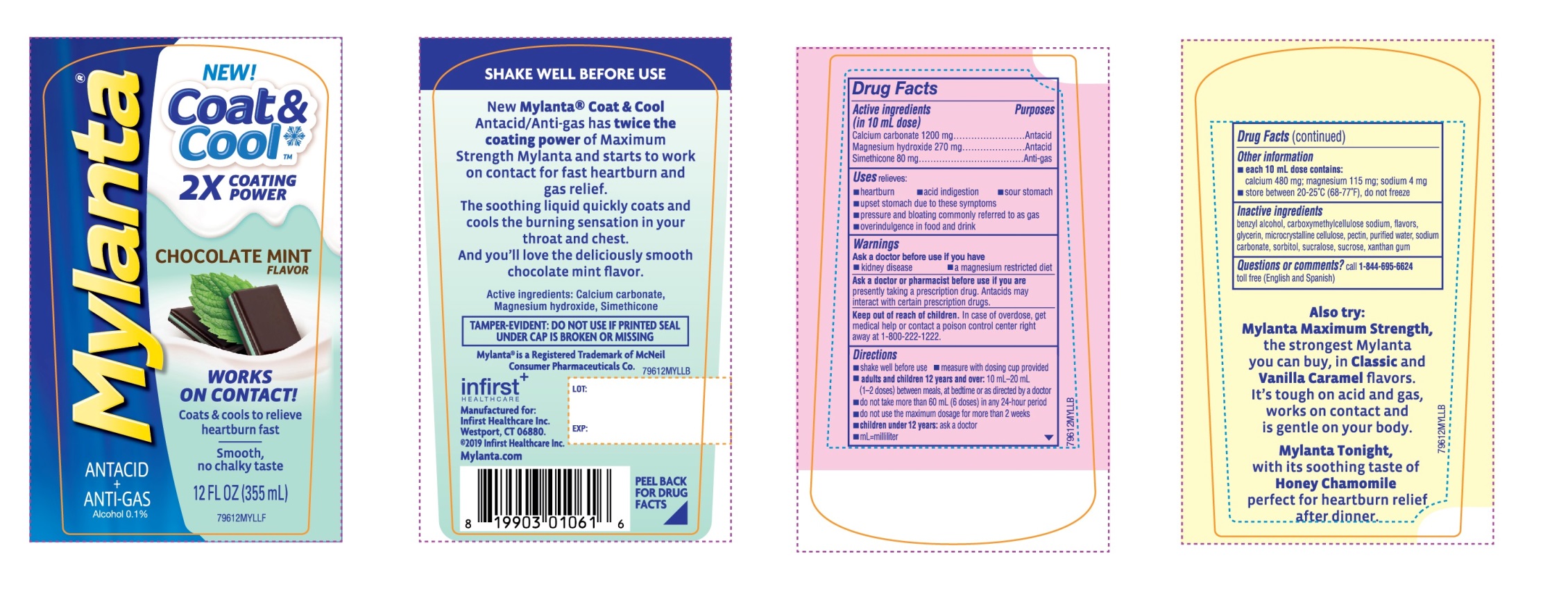 DRUG LABEL: Mylanta Coat and Cool
NDC: 62372-796 | Form: LIQUID
Manufacturer: INFIRST HEALTHCARE INC.
Category: otc | Type: HUMAN OTC DRUG LABEL
Date: 20240101

ACTIVE INGREDIENTS: CALCIUM CARBONATE 1200 mg/10 mL; MAGNESIUM HYDROXIDE 270 mg/10 mL; DIMETHICONE 80 mg/10 mL
INACTIVE INGREDIENTS: BENZYL ALCOHOL; CARBOXYMETHYLCELLULOSE SODIUM, UNSPECIFIED FORM; GLYCERIN; MICROCRYSTALLINE CELLULOSE; PECTIN; WATER; SODIUM CARBONATE; SORBITOL; SUCRALOSE; SUCROSE; XANTHAN GUM

Mylanta Coat & Cool Drug Facts

Active ingredient (in 10 mL dose)

Calcium Carbonate 1200 mg

Magnesium Hydroxide 270 mg

Simethicone 80 mg

Purpose

Antacid

Antacid

Anti-gas

Uses

- relieves:
  - acid indigestion
  - heartburn
  - sour stomach
  - upset stomach due to these symptoms
  - pressure and bloating commonly referred to as gas
  - overindulgence in food and drink

Warnings

Ask a doctor before use if you have

- kidney disease
- a magnesium-restricted diet

ask a doctor or pharmacist before use if you are

presently taking a prescription drug. Antacids may interact with certain prescription drugs.

Keep out of reach of children.

In case of overdose, get medical help or contact a Poison Control Center right away at (1-800-222-1222)

Directions

- shake well before using
- Measure with dosing cup provided
- adults and children12 years and over:take 10-20 mL (1-2 doses) between meals, at bedtime, or as directed by a doctor
- do not take more than 60 mL in 24 hours period
- do not use the maximum dosage for more than 2 weeks
- children under 12 years:ask a doctor
- mL-milliliter

Other information

- each 10 mL dose contains:calcium 480 mg; magnesium 115 mg; sodium 4 mg
- store between 20-25°C (68-77°F), do not freeze.

Inactive ingredients

benzyl alcohol, carboxymethylcellulose sodium, flavor, glycerin, microcrystalline cellulose, purified water, sodium carbonate, sorbitol, sucralose, sucrose, xanthan gum

Questions or comments?

Call 1-844-695-6624 toll free (English and Spanish)

Principal Display Panel

Mylanta®

NDC# 62372-796-12

NEW! Coat & Cool™

2X COATING POWER

CHOCOLATE MINT FLAVOR

WORKS ON CONTACT!

Coats & cools to relieve heartburn fast

Smooth chalky taste

12 FL OZ (355 mL)

TAMPER EVIDENT: DO NOT USE IF PRINTED SAFETY SEAL AROUND OR UNDER CAP IS BROKEN OR MISSING.

Mylanta® is Registered Trademark of McNeil Consumer Pharmaceuticals Co.

Infirst

HEALTHCARE

Manufactured for:

Infirst Healthcare Inc.

Westport, CT 06880

© 2019 Infirst Healthcare Inc.

Mylanta.com